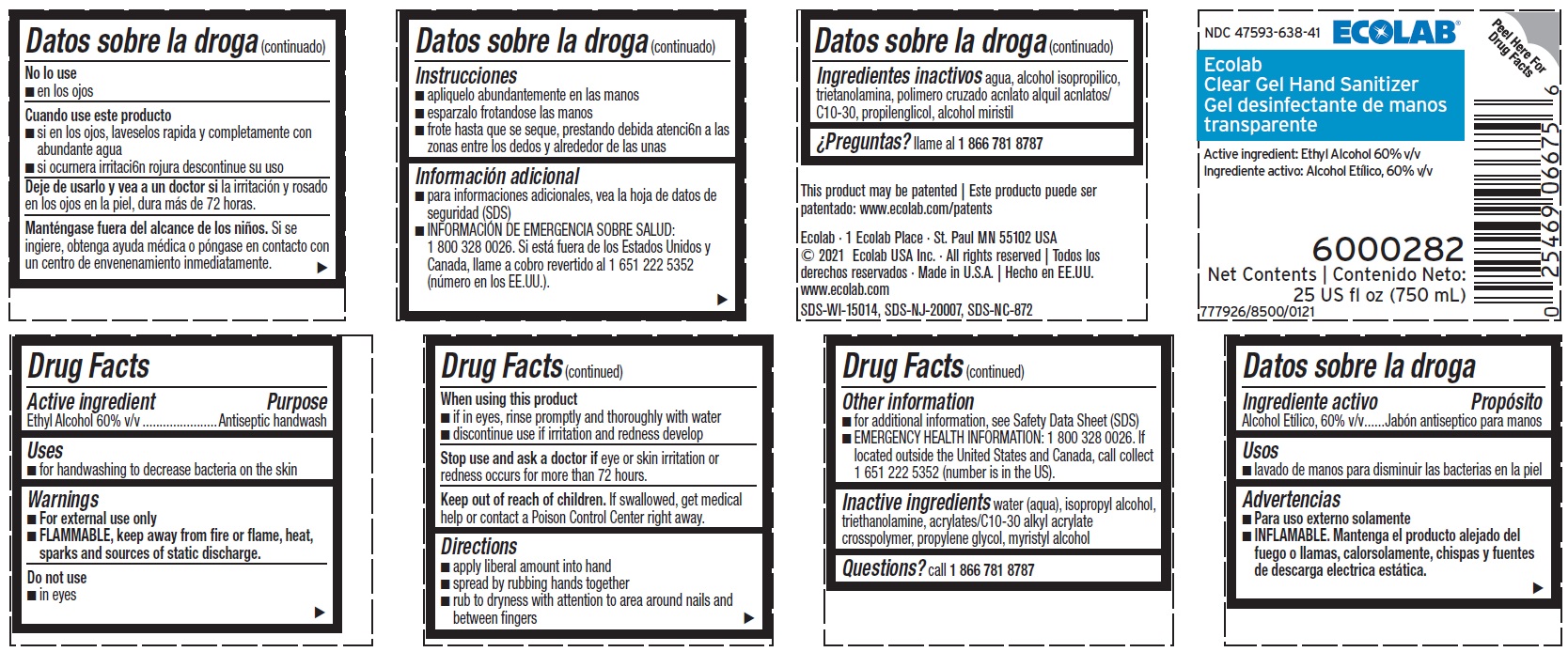 DRUG LABEL: ECOLAB CLEAR
NDC: 47593-638 | Form: LIQUID
Manufacturer: Ecolab Inc.
Category: otc | Type: HUMAN OTC DRUG LABEL
Date: 20240806

ACTIVE INGREDIENTS: ALCOHOL 60 mL/100 mL
INACTIVE INGREDIENTS: ISOPROPYL ALCOHOL; TROLAMINE; CARBOMER COPOLYMER TYPE B (ALLYL PENTAERYTHRITOL CROSSLINKED); Propylene glycol; MYRISTYL ALCOHOL

Drug Facts

Active ingredient

Ethyl Alcohol 60% v/v

Purpose

Antiseptic handwash

Uses

- For handwashing to decrease bacteria on the skin

Warnings

- For external use only
- FLAMMABLE, keep away from fire or flame, heat, sparks and sources of static discharge

Do not use

- In eyes

When using this product

- If in eyes, rinse promptly and thoroughly with water
- Discontinue use if irritation and redness develop

Stop use and ask a doctor if eye or skin irritation or redness occurs for more than 72 hours

Keep out of reach of children. If swallowed, get medical help or contact a Poison Control Center right away.

Directions

- Apply liberal amount into hand
- Spread by rubbing hands together
- Rub to dryness with attention to area around nails and between fingers

Other information

- For additional information, see Safety Data Sheet (SDS)
- EMERGENCY HEALTH INFORMATION: 1 800 328 0026. If located outside the United States and Canada, call collect 1 651 222 5352 (number is in the US).

INACTIVE INGREDIENT

Inactive ingredients water (aqua), isopropyl alcohol, triethanolamine, acrylates/C10-30 alkyl acrylate crosspolymer, propylene glycol, myristyl alcohol

Questions? call 1 866 781 8787

Principal display panel and representative label

NDC 47593-638-41 ECOLAB

Ecolab

Clear Gel Hand Sanitizer

Active ingredient: Ethyl Alochol 60% v/v

6000282

Net Contents

25 US fl oz (750 mL)

777926/850121

This product may be patented: www.ecolab.com/patents

Ecolab · 1 Ecolab Place · St. Paul MN 55102 USA

© 2021 Ecolab USA Inc. · All rights reserved

Made in U.S.A.

www.ecolab.com

SDS-WI-15014, SDS-NJ-20007, SDS-NC-872